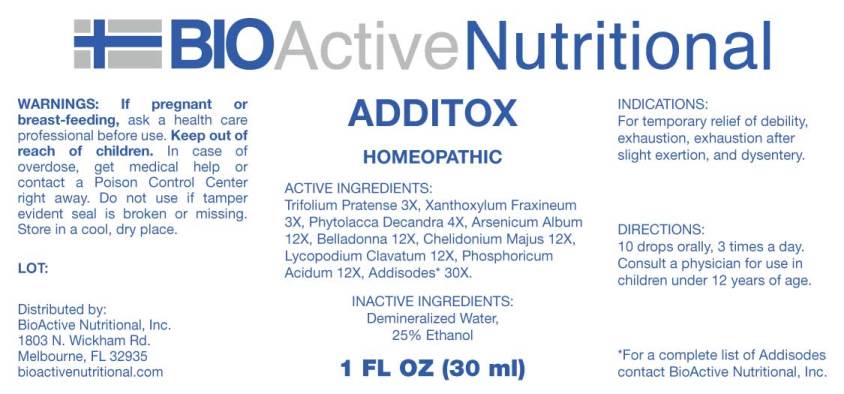 DRUG LABEL: Additox
NDC: 43857-0487 | Form: LIQUID
Manufacturer: BioActive Nutritional, Inc.
Category: homeopathic | Type: HUMAN OTC DRUG LABEL
Date: 20180718

ACTIVE INGREDIENTS: TRIFOLIUM PRATENSE FLOWER 3 [hp_X]/1 mL; ZANTHOXYLUM AMERICANUM BARK 3 [hp_X]/1 mL; PHYTOLACCA AMERICANA ROOT 4 [hp_X]/1 mL; ARSENIC TRIOXIDE 12 [hp_X]/1 mL; ATROPA BELLADONNA 12 [hp_X]/1 mL; CHELIDONIUM MAJUS 12 [hp_X]/1 mL; LYCOPODIUM CLAVATUM SPORE 12 [hp_X]/1 mL; PHOSPHORIC ACID 12 [hp_X]/1 mL; ASPARTAME 30 [hp_X]/1 mL; BENZALKONIUM CHLORIDE 30 [hp_X]/1 mL; FORMALDEHYDE 30 [hp_X]/1 mL; METHYLENE CHLORIDE 30 [hp_X]/1 mL; METHYLPARABEN 30 [hp_X]/1 mL; PROPYLPARABEN 30 [hp_X]/1 mL; SODIUM BENZOATE 30 [hp_X]/1 mL; SODIUM CITRATE 30 [hp_X]/1 mL; TITANIUM DIOXIDE 30 [hp_X]/1 mL; ZINC OXIDE 30 [hp_X]/1 mL
INACTIVE INGREDIENTS: WATER; ALCOHOL

Drug Facts:

ACTIVE INGREDIENTS:

Trifolium Pratense 3X, Xanthoxylum Fraxineum 3X, Phytolacca Decandra 4X, Arsenicum Album 12X, Belladonna 12X, Chelidonium Majus 12X, Lycopodium Clavatum 12X, Phosphoricum Acidum 12X, Aspartame 30X, Benzalkonium Chloride 30X, Formalinum 30X, Methylene Chloride 30X, Methylparaben 30X, Propylparaben 30X, Sodium Benzoate 30X, Sodium Citrate 30X, Titanium Dioxide 30X.

INDICATIONS:

For temporary relief of debility, exhaustion, exhaustion after slight exertion, and dysentery.

WARNINGS:

If pregnant or breast-feeding, ask a health care professional before use.

Keep out of reach of children. In case of overdose, get medical help or contact a Poison Control Center right away.

Do not use if tamper evident seal is broken or missing.

Store in cool, dry place.

DIRECTIONS:

10 drops orally, 3 times a day. Consult a physician for use in children under 12 years of age.

INACTIVE INGREDIENTS:

Demineralized Water, 25% Ethanol.

INDICATIONS:

For temporary relief of debility, exhaustion, exhaustion after slight exertion, and dysentery.

INACTIVE INGREDIENTS:

Demineralized Water, 25% Ethanol.

QUESTIONS:

Distributed by:
BioActive Nutritional, Inc.
1803 N. Wickham Rd.
Melbourne, FL 32935
bioactivenutritional.com

*For a complete list of Addisodes contact BioActive Nutritional, Inc.

PACKAGE LABEL DISPLAY:

BIOActive Nutritional

ADDITOX

HOMEOPATHIC

1 FL OZ (30 ml)